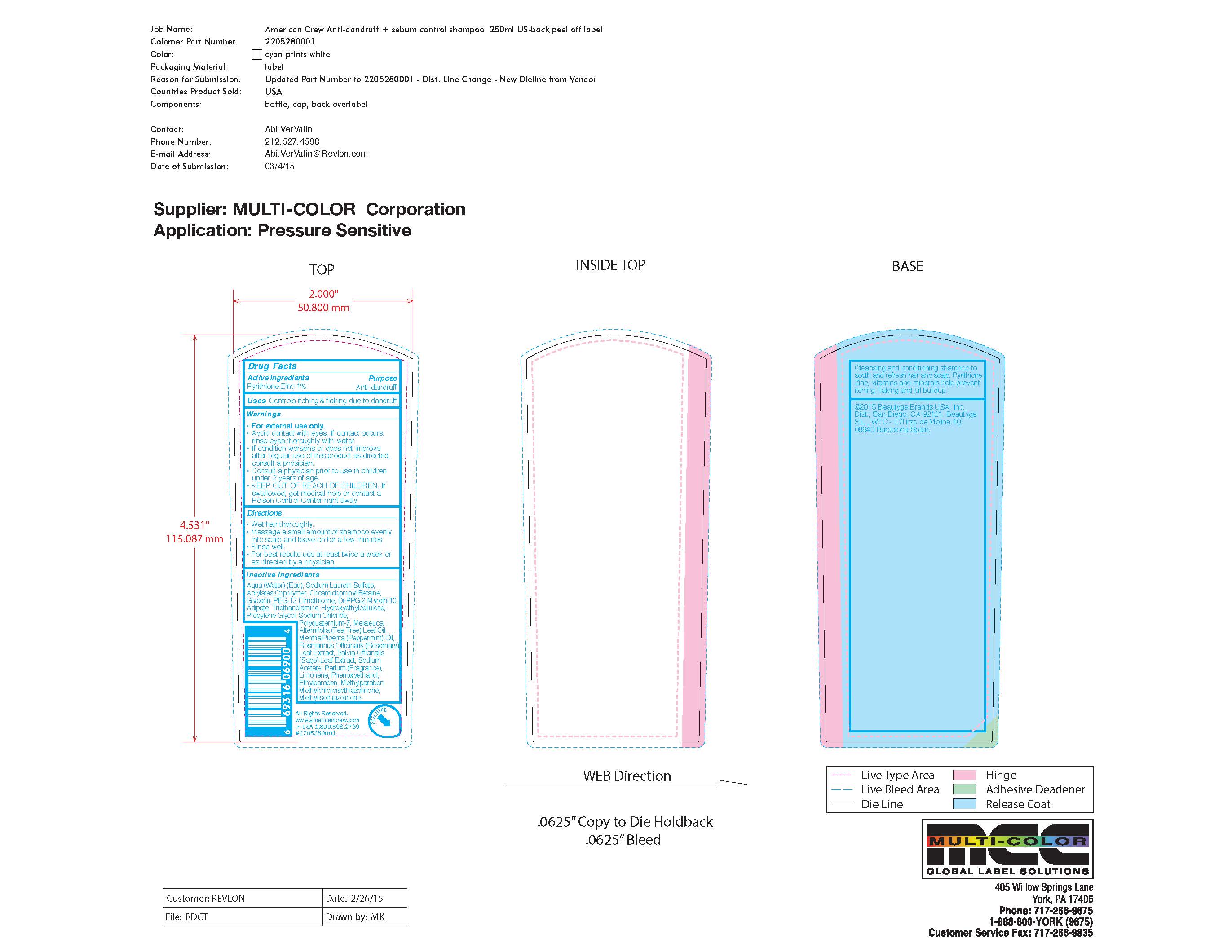 DRUG LABEL: American Crew
NDC: 10967-650 | Form: SHAMPOO
Manufacturer: Revlon Consumer Products Corp
Category: otc | Type: HUMAN OTC DRUG LABEL
Date: 20241230

ACTIVE INGREDIENTS: PYRITHIONE ZINC 1 mg/1 mL
INACTIVE INGREDIENTS: CAPRYLYL GLYCOL; DECYL GLUCOSIDE; MENTHOL; WATER; AMMONIUM LAURYL SULFATE; COCAMIDOPROPYL BETAINE; DI-PPG-2 MYRETH-10 ADIPATE; SODIUM CHLORIDE; SODIUM HYDROXIDE; PHENOXYETHANOL; BUTYL ACRYLATE/METHYL METHACRYLATE/METHACRYLIC ACID COPOLYMER (18000 MW); CITRIC ACID; HYDROXYPROPYL GUAR HYDROXYPROPYLTRIMONIUM CHLORIDE; LAURYL GLUCOSIDE; PEG-150 DISTEARATE; PANTHENOL

American Crew 2-In-1 Anti-Dandruff & Sebum Control Shampoo

Active Ingredients:

Pyrithione Zinc 1%

Purpose

Anti Dandruff

Uses:

Controls itching & flaking due to dandruff.

Warnings:

For external use only.
• Avoid contact with eyes. If contact occurs,
rinse eyes thoroughly with water.
• If condition worsens or does not improve
after regular use of this product as directed,
consult a physician.
• Consult a physician prior to use in children
under 2 years of age.
• KEEP OUT OF REACH OF CHILDREN. If
swallowed, get medical help or contact a
Poison Control Center right away.

Directions

• Wet hair thoroughly.
• Massage a small amount of shampoo evenly
into scalp and leave on for a few minutes.
• Rinse well.
• For best results use at least twice a week or
as directed by a physician.

Inactive Ingredients

Aqua (Water) (Eau), Sodium Laureth Sulfate,
Acrylates Copolymer, Cocamidopropyl Betaine,
Glycerin, PEG-12 Dimethicone, Di-PPG-2 Myreth-10
Adipate, Triethanolamine, Hydroxyethylcellulose,
Propylene Glycol, Sodium Chloride,
Polyquaternium-7, Melaleuca
Alternifolia (Tea Tree) Leaf Oil,
Mentha Piperita (Peppermint) Oil,
Rosmarinus Officinalis (Rosemary)
Leaf Extract, Salvia Officinalis
(Sage) Leaf Extract, Sodium
Acetate, Parfum (Fragrance),
Limonene, Phenoxyethanol,
Ethylparaben, Methylparaben

Label

American Crew 2-In-1 Anti-Dandruff & Sebum Control Shampoo